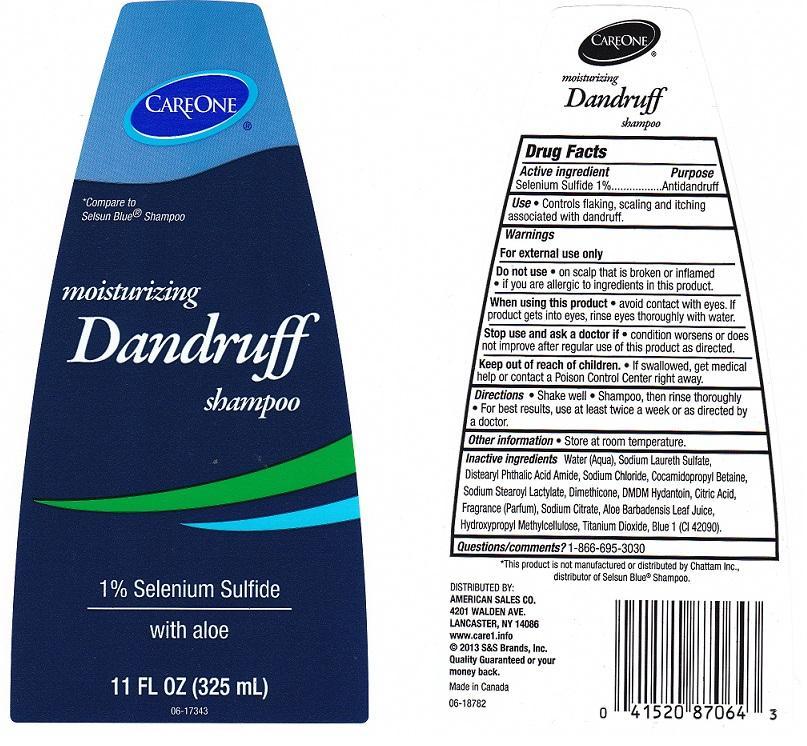 DRUG LABEL: CARE ONE
NDC: 41520-621 | Form: LIQUID
Manufacturer: AMERICAN SALES COMPANY
Category: otc | Type: HUMAN OTC DRUG LABEL
Date: 20130715

ACTIVE INGREDIENTS: SELENIUM SULFIDE 10 mg/1 mL
INACTIVE INGREDIENTS: WATER; SODIUM LAURETH SULFATE; DISTEARYL PHTHALAMIC ACID; SODIUM CHLORIDE; COCAMIDOPROPYL BETAINE; SODIUM STEAROYL LACTYLATE; DIMETHICONE; DMDM HYDANTOIN; CITRIC ACID MONOHYDRATE; SODIUM CITRATE; ALOE VERA LEAF; HYPROMELLOSES; TITANIUM DIOXIDE; FD&C BLUE NO. 1

DRUG FACTS

ACTIVE INGREDIENT

SELENIUM SULFIDE 1%

PURPOSE

ANTIDANDRUFF

USE

CONTROLS FLAKING, SCALING AND ITCHING ASSOCIATED WITH DANDRUFF.

WARNINGS

FOR EXTERNAL USE ONLY.

DO NOT USE

ON SCALP THAT IS BROKEN OR INFLAMED, IF YOU ARE ALLERGIC TO INGREDIENTS IN THIS PRODUCT.

WHEN USING THIS PRODUCT

AVOID CONTACT WITH EYES. IF PRODUCT GETS INTO EYES, RINSE EYES THOROUGHLY WITH WATER.

STOP USE AND ASK A DOCTOR IF

CONDITION WORSENS OR DOES NOT IMPROVE AFTER REGULAR USE OF THIS PRODUCT AS DIRECTED.

KEEP OUT OF REACH OF CHILDREN

IF SWALLOWED, GET MEDICAL HELP OR CONTACT A POISON CONTROL CENTER RIGHT AWAY.

DIRECTIONS

SHAKE WELL. SHAMPOO, THEN RINSE THOROUGHLY. FOR BEST RESULTS, USE AT LEAST TWICE A WEEK OR AS DIRECTED BY A DOCTOR.

OTHER INFORMATION

STORE AT ROOM TEMPERATURE.

INACTIVE INGREDIENTS:

WATER (AQUA), SODIUM LAURETH SULFATE, DISTEARYL PHTHALIC ACID AMIDE, SODIUM CHLORIDE, COCAMIDOPROPYL BETAINE, SODIUM STEAROYL LACTYLATE, DIMETHICONE, DMDM HYDANTOIN, CITRIC ACID, FRAGRANCE (PARFUM), SODIUM CITRATE, ALOE BARBADENSIS LEAF JUICE, HYDROXYPROPYL METHYLCELLULOSE, TITANIUM DIOXIDE, BLUE 1 (CI 42090).

QUESTIONS/COMMENTS?

1-866-695-3030